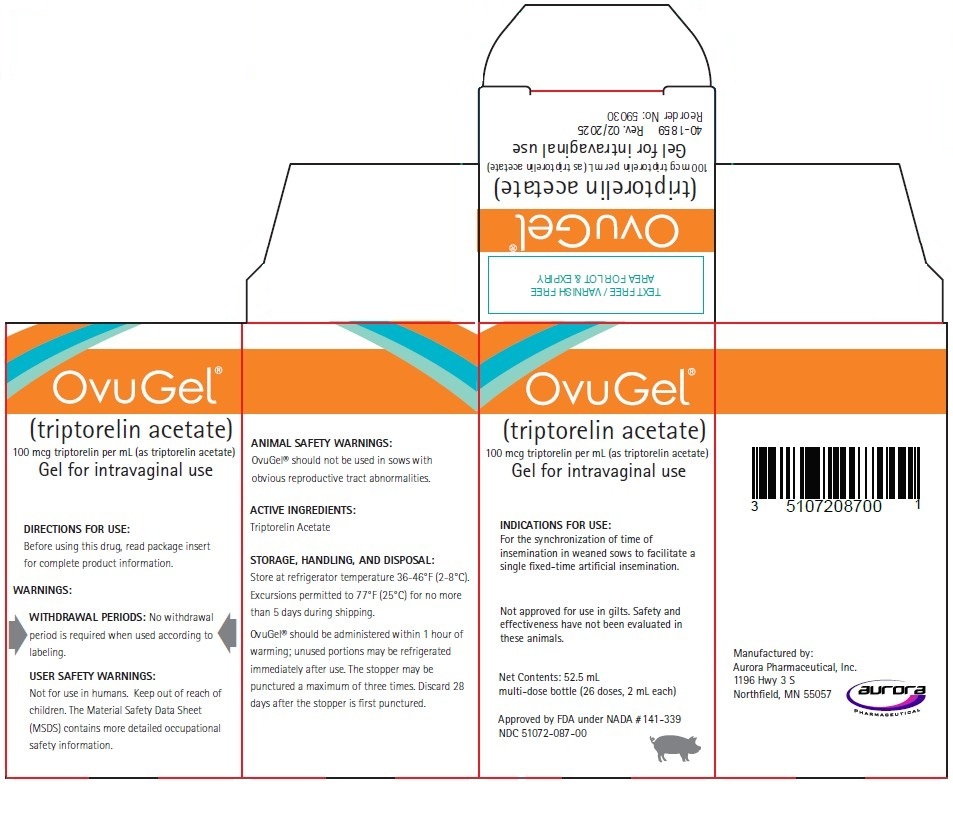 DRUG LABEL: OvuGel
NDC: 51072-087 | Form: GEL
Manufacturer: Aurora Pharmaceutical, Inc.
Category: animal | Type: OTC ANIMAL DRUG LABEL
Date: 20260122

ACTIVE INGREDIENTS: Triptorelin Acetate 100 ug/1 mL

OvuGel®

ACTIVE INGREDIENT:

triptorelin acetate

DOSAGE FORM & STRENGTH:

100 mcg triptorelin per mL (as triptorelin acetate)
Gel for intravaginal use

INDICATIONS FOR USE:

For the synchronization of time of insemination in weaned sows to facilitate a single fixed-time artificial insemination. Not approved for use in gilts. Safety and effectiveness have not been evaluated in these animals.

DESCRIPTION:

OvuGel® is a thin, clear to slightly hazy gel. Each mL of OvuGel® contains 100 mcg of triptorelin (as triptorelin acetate) for intravaginal administration.

WARNINGS:

WITHDRAWAL PERIOD:

No withdrawal period is required when used according to labeling.
USER SAFETY WARNINGS:

Not for Use in Humans. Keep Out of Reach of Children. The Material Safety Data Sheet (MSDS) contains more detailed occupational safety information.
ANIMAL SAFETY WARNINGS:

OvuGel® should not be used in sows with obvious reproductive tract abnormalities.

RECOMMENDATIONS FOR SAFE AND EFFECTIVE USE:

Use of a bottle mount multi-dose applicator is recommended to ensure accurate dosing.
The use of adequate sperm numbers per insemination and proper semen storage, as recommended by the semen or artificial inseminator catheter suppliers, is recommended.

DIRECTIONS FOR USE:

OvuGel® should be administered intravaginally at approximately 96 hours after weaning. The product should be warmed at room temperature for a minimum of 10 minutes prior to use. Insert the delivery tube into the vagina so that the tip rests 1/2 inch (1-3 cm) posterior to the cervix. Use a separate sheath over the delivery tube for each sow treated. Each sow should receive a single 2 mL dose of OvuGel®. Sows should be inseminated 22 +/- 2 hours following administration of OvuGel® using standard artificial insemination techniques. Sows should be exposed to a boar during time of insemination. (See end of package insert for more detailed directions for OvuGel® administration).

STORAGE, HANDLING, AND DISPOSAL:

Store at refrigerator temperature 36-46°F (2-8°C). Excursions permitted to 77°F (25°C) for no more than 5 days during shipping.
OvuGel® should be administered within 1 hour of warming; unused portions may be refrigerated immediately after use. The bottle stopper may be punctured a maximum of three times. Discard 28 days after the stopper is first punctured.

HOW SUPPLIED:

OvuGel® is available in 52.5 mL multi-dose bottle.

QUESTIONS/COMMENTS

To obtain an MSDS, for technical assistance, or to report adverse events, contact Aurora Pharmaceutical at 1-888-215-1256 or www.aurorapharmaceutical.com. For additional information about adverse drug experience reporting for animal drugs, contact FDA at 1-888-FDA-VETS, or www.fda.gov/reportanimalae.

Approved by FDA under NADA #141-339
NDC 51072-087-00

PACKAGE LABEL

Principal Display Panel – 52.5 mL Bottle Carton
OvuGel®
(triptorelin acetate)
100 mcg triptorelin per mL (as triptorelin acetate)
Gel for intravaginal use

INDICATIONS FOR USE:
For the synchronization of time of insemination in weaned sows to facilitate a single fixed-time artificial insemination.

Not approved for use in gilts. Safety and effectiveness have not been evaluated in these animals.

Net Contents: 52.5 mL
multi-dose bottle (26 doses, 2 mL each)

Approved by FDA under NADA # 141-339
NDC 51072-087-00

Manufactured by: Aurora Pharmaceutical, Inc.
1196 Hwy 3 S
Northfield, MN 55057

IN 40-1859 Rev. 02/2025
Reorder No: 59030